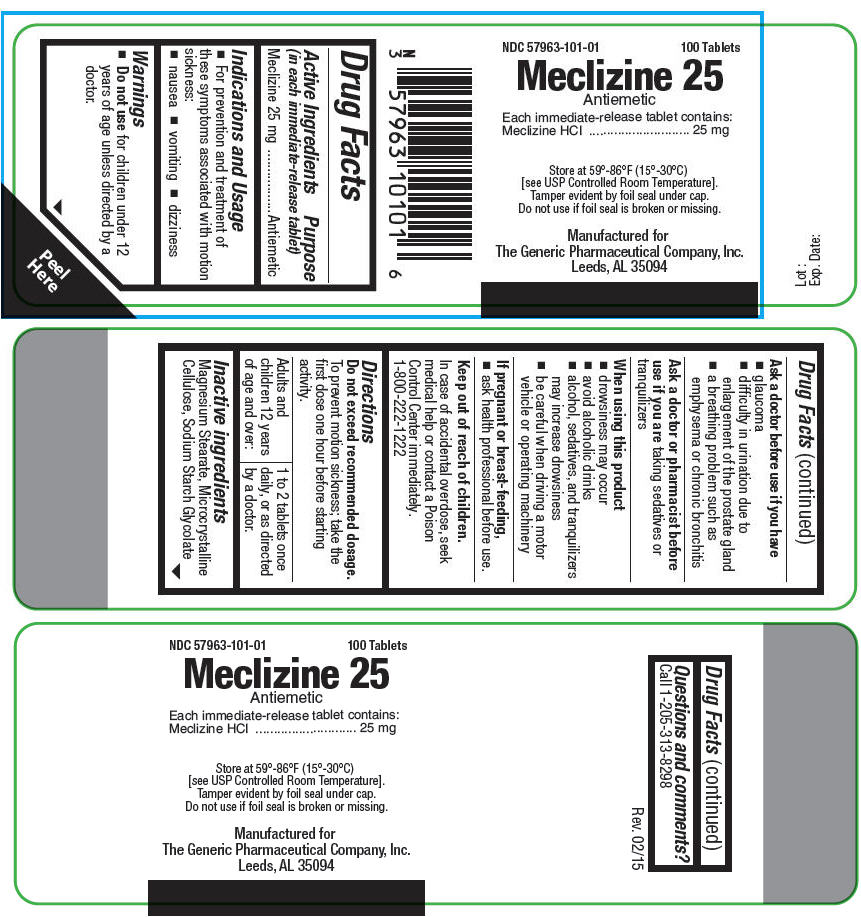 DRUG LABEL: Meclizine 25
NDC: 57963-101 | Form: TABLET
Manufacturer: The Generic Pharmaceutical Company
Category: otc | Type: HUMAN OTC DRUG LABEL
Date: 20170109

ACTIVE INGREDIENTS: MECLIZINE HYDROCHLORIDE 25 mg/1 1
INACTIVE INGREDIENTS: Magnesium Stearate; Microcrystalline Cellulose; SODIUM STARCH GLYCOLATE TYPE A POTATO

Meclizine 25

Drug Facts

Active Ingredients (in each immediate-release tablet)

Meclizine 25 mg

Purpose

Antiemetic

Indications and Usage

- For prevention and treatment of these symptoms associated with motion sickness:
  - nausea
  - vomiting
  - dizziness

Warnings

- Do not use for children under 12 years of age unless directed by a doctor.

Ask a doctor before use if you have

- glaucoma
- difficulty in urination due to enlargement of the prostate gland
- a breathing problem such as emphysema or chronic bronchitis

Ask a doctor or pharmacist before use if you are taking sedatives or tranquilizers

When using this product

- drowsiness may occur
- avoid alcoholic drinks
- alcohol, sedatives, and tranquilizers may increase drowsiness
- be careful when driving a motor vehicle or operating machinery

If pregnant or breast-feeding,

- ask health professional before use.

Keep out of reach of children.

In case of accidental overdose, seek medical help or contact a Poison Control Center immediately. 1-800-222-1222

Directions

Do not exceed recommended dosage.

To prevent motion sickness; take the first dose one hour before starting activity.

Adults and children 12 years of age and over: | 1 to 2 tablets once daily, or as directed by a doctor.

Inactive ingredients

Magnesium Stearate, Microcrystalline Cellulose, Sodium Starch Glycolate

Questions and comments?

Call 1-205-313-8298

Manufactured for
The Generic Pharmaceutical Company, Inc.
Leeds, AL 35094

PRINCIPAL DISPLAY PANEL - 25 mg Tablet Bottle Label

NDC 57963-101-01
100 Tablets

Meclizine 25
Antiemetic

Each immediate-release tablet contains:
Meclizine HCl
25 mg

Store at 59°-86°F (15°-30°C)
[see USP Controlled Room Temperature].
Tamper evident by foil seal under cap.
Do not use if foil seal is broken or missing.

Manufactured for
The Generic Pharmaceutical Company, Inc.
Leeds, AL 35094